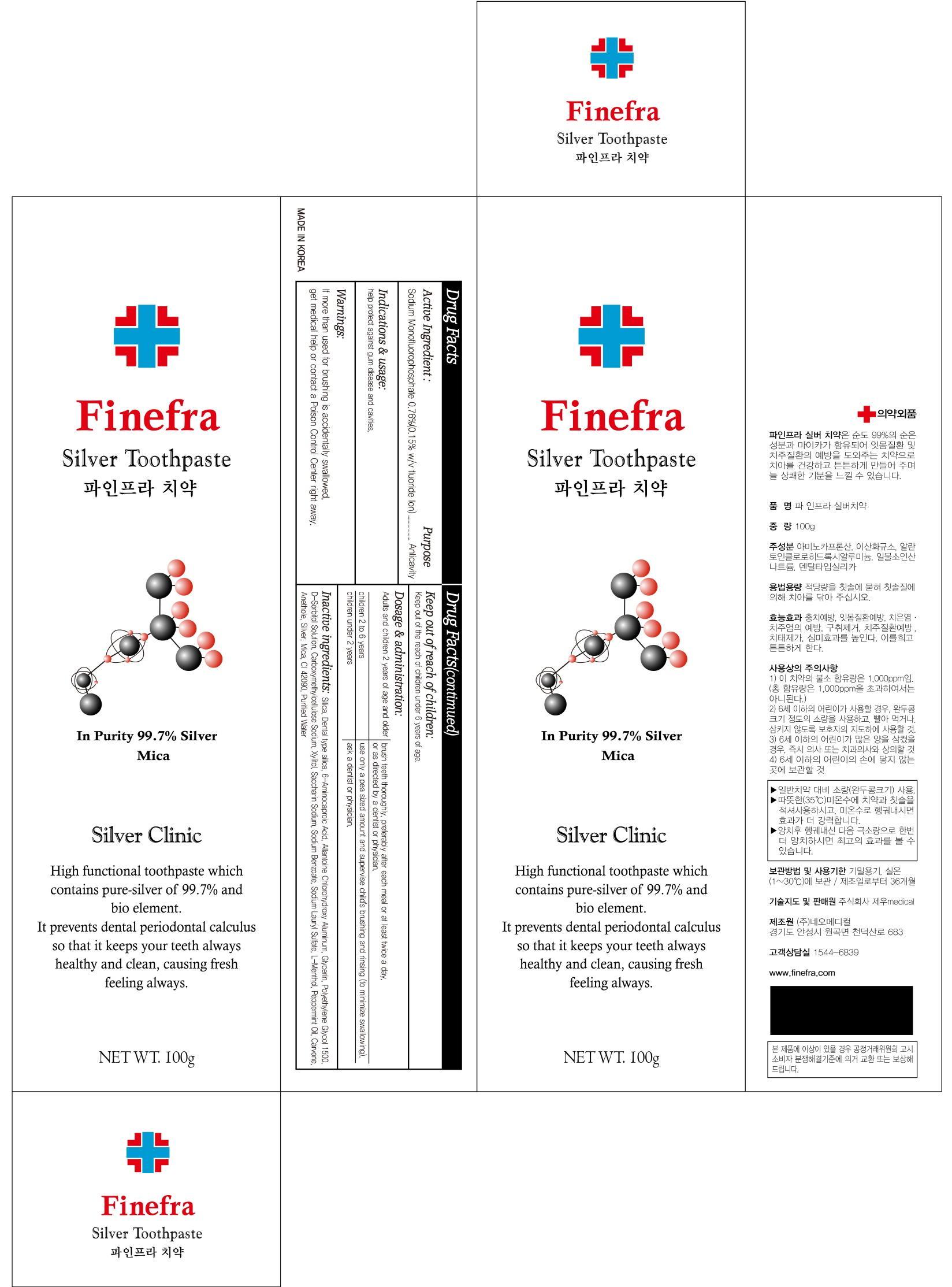 DRUG LABEL: Finefra Silver
NDC: 69653-020 | Form: PASTE, DENTIFRICE
Manufacturer: Jewoo Medical Co,.Ltd
Category: otc | Type: HUMAN OTC DRUG LABEL
Date: 20181129

ACTIVE INGREDIENTS: Sodium Monofluorophosphate 0.76 g/100 g
INACTIVE INGREDIENTS: Glycerin

ACTIVE INGREDIENT

Active ingredient: Sodium Monofluorophosphate 0.76%

INACTIVE INGREDIENT

Inactive ingredients: Silica, Dental type silica, 6-Aminocaproic Acid, Allantoine Chlorohydroxy Aluminum, Glycerin, Polyethylene Glycol 1500, D-Sorbitol Solution, Carboxymethylcellulose Sodium, Xylitol, Saccharin Sodium, Sodium Benzoate, Sodium Lauryl Sulfate, L-Menthol, Peppermint Oil, Carvone, Anethole, Silver, Mica, CI 42090, Purified Water

PURPOSE

Purpose : Anticavity

WARNINGS

Warnings: If more than used for brushing is accidentally swallowed, get medical help or contact a Poison Control Center right away.

Keep out of reach of children: Keep out of the reach of children under 6 years of age.

INDICATIONS & USAGE

Indications & usage: help protect against gum disease and cavities.

DOSAGE & ADMINISTRATION

Dosage & administration: adults and children 2 years of age and older: brush teeth thoroughly, preferably after each meal or at least twice a day, or as directed by a dentist or physician. children 2 to 6 years: use only a pea sized amount and supervise child's brushing and rinsing (to minimize swallowing). children under 2 years: ask a dentist or physician.